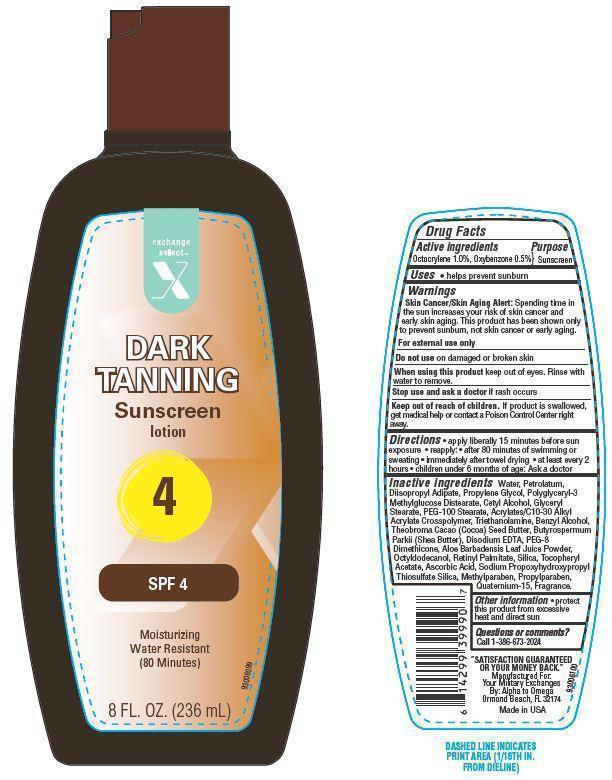 DRUG LABEL: Exchange Select Dark Tanning Sunscreen
NDC: 55301-005 | Form: LOTION
Manufacturer: ARMY AND AIR FORCE EXCHANGE SERVICE
Category: otc | Type: HUMAN OTC DRUG LABEL
Date: 20131025

ACTIVE INGREDIENTS: OCTOCRYLENE 1 g/100 g; OXYBENZONE 0.5 g/100 g
INACTIVE INGREDIENTS: WATER; PETROLATUM; DIISOPROPYL ADIPATE; PROPYLENE GLYCOL; SILICON DIOXIDE; CETYL ALCOHOL; GLYCERYL MONOSTEARATE; TROLAMINE; PEG-100 STEARATE; .ALPHA.-TOCOPHEROL ACETATE; EDETATE DISODIUM; BENZYL ALCOHOL; COCOA BUTTER; SHEA BUTTER; PEG-8 DIMETHICONE; ALOE VERA LEAF; OCTYLDODECANOL; VITAMIN A PALMITATE; ASCORBIC ACID; METHYLPARABEN; PROPYLPARABEN; QUATERNIUM-15

Drug Facts

Active ingredients

Octocrylene 1.0%

Oxybenzone 0.5 %

Purpose

Sunscreen

Uses

- helps prevent sunburn

Warnings

Skin Cancer/Skin Aging Alert: Spending time in the sun increases your risk of skin cancer and early skin aging. This product has been shown only to prevent sunburn, not skin cancer or early aging.

For external use only. Do not use on damaged or broken skin.

When using this product

- keep out of eyes. Rinse with water to remove

Stop use and ask a doctor if

- rash occurs.

Keep Out of the reach of children.

If swallowed get medical help or contact a Poison Control Center right away.

Directions

- apply liberally 15 minutes before sun exposure
- reapply:
- after 80 minutes of swimming or sweating
- immediately after towel drying
- at least every 2 hours
- children under 6 months of age: Ask a doctor

Other information

- protect this product from excessive heat and direct sun

Inactive ingredients

Water, Petrolatum, Diisopropyl Adipate, Propylene Glycol, Polyglyceryl-3 Methylglucose Distearate, Cetyl Alcohol, Glyceryl Stearate, PEG-100 Stearate, Acrylates/C10-30 Alkyl Acrylate Crosspolymer, Triethanolamine, Benzyl Alcohol, Theobroma Cacao (Cocoa) Seed Butter, Butyrospermum Parkii (Shea) Butter, Disodium EDTA, PEG-8 Dimethicone, Aloe Barbadensis Leaf Juice Powder, Octyldodecanol, Retinyl Palmitate, Silica, Tocopheryl Acetate, Ascorbic Acid, Sodium Propoxyhydroxypropyl Thiosulfate Silica, Methylparaben, Propylparaben, Quaternium-15, Fragrance.

Principal Display Panel

exchange

select

X

Sunscreen lotion

4

SPF 4

Moisturing

Water Resistant

(80 Minutes)

8 FL. OZ. (236 mL)

Questions or comments?

Call 1-396-673-2024